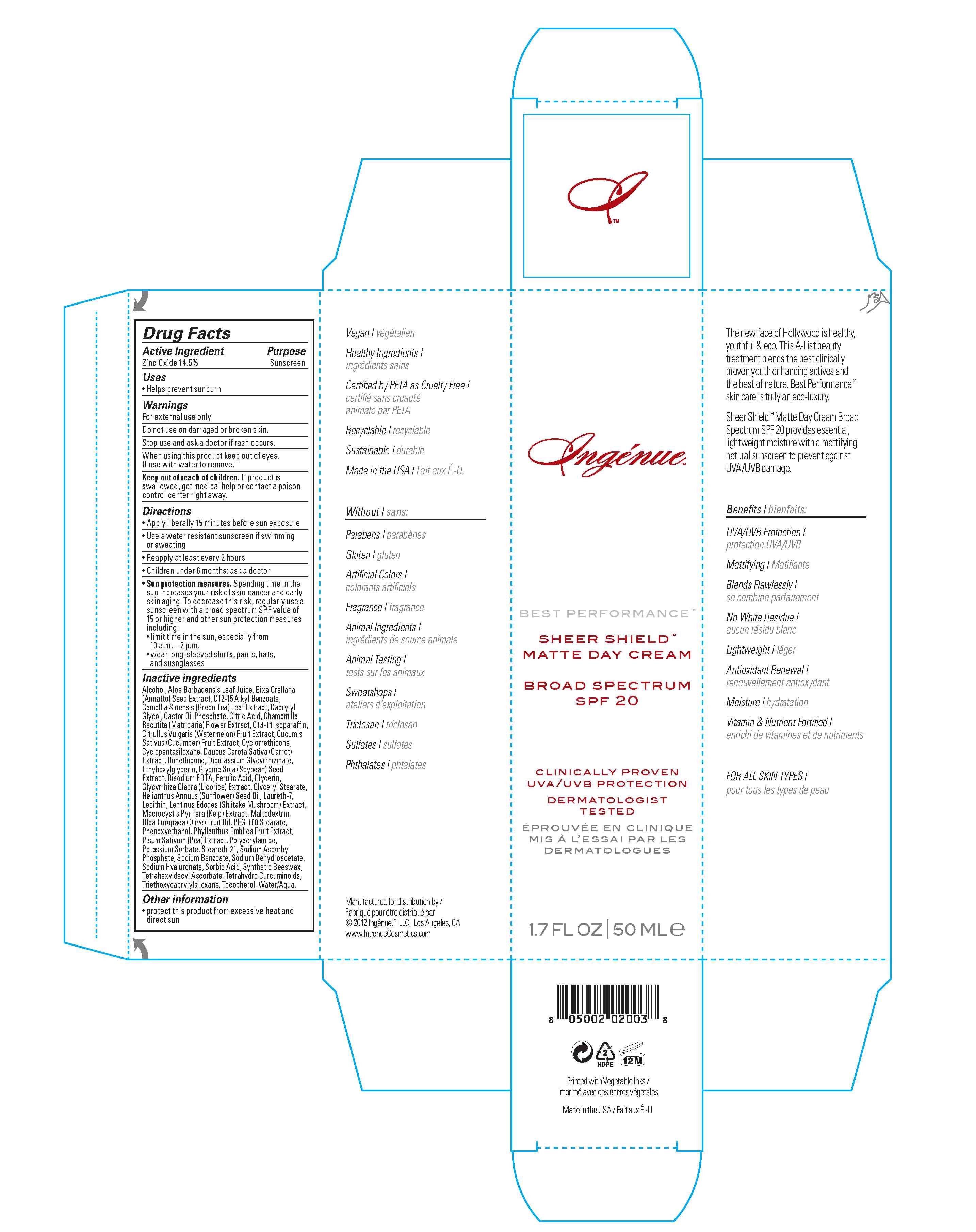 DRUG LABEL: Ingenue
NDC: 54151-101 | Form: CREAM
Manufacturer: Ingenue, LLC
Category: otc | Type: HUMAN OTC DRUG LABEL
Date: 20121203

ACTIVE INGREDIENTS: ZINC OXIDE 14.5 mg/1 mL
INACTIVE INGREDIENTS: ALOE VERA LEAF; ALKYL (C12-15) BENZOATE; GLYCERIN; C13-14 ISOPARAFFIN; CYCLOMETHICONE; GLYCERYL MONOSTEARATE; LAURETH-7; PEG-100 STEARATE; POLYACRYLAMIDE (10000 MW); WATERMELON; STEARETH-21; SYNTHETIC WAX (1800 MW); DIMETHICONE; OLIVE OIL; SUNFLOWER OIL; GREEN TEA LEAF; CHAMOMILE; CUCUMBER; CARROT; GLYCYRRHIZA GLABRA; LENTINULA EDODES MYCELIUM; MACROCYSTIS PYRIFERA; PEA; CAPRYLYL GLYCOL; CASTOR OIL; SODIUM BENZOATE; POTASSIUM SORBATE; ANNATTO; GLYCYRRHIZINATE DIPOTASSIUM; EDETATE DISODIUM; FERULIC ACID; MALTODEXTRIN; PHYLLANTHUS EMBLICA FRUIT; HYALURONATE SODIUM; TETRAHYDRODIFERULOYLMETHANE; SORBIC ACID; TETRAHEXYLDECYL ASCORBATE; ASCORBYL PALMITATE; TOCOPHEROL; SODIUM DEHYDROACETATE; PHENOXYETHANOL; WATER; ALCOHOL; CYCLOMETHICONE 5; CITRIC ACID MONOHYDRATE; ETHYLHEXYLGLYCERIN; SOYBEAN; EGG PHOSPHOLIPIDS; TRIETHOXYCAPRYLYLSILANE

Drug Facts

Active Ingredient:

Zinc Oxide 14.5%

Purpose:

Sunscreen

Keep out of reach of children. If product is swallowed, get medical help or contact a poison control center right away.

Uses:

Helps prevent sunburn

Warnings:

- For external use only
- Do not use on damaged or broken skin.
- Stop use and ask a doctor if rash occurs.
- When using this product keep out of eyes. Rinse with water to remove.

Directions:

Apply liberally 15 minutes before sun exposure
Use a water resistant sunscreen if swimming or sweating
Reapply at least every 2 hours
Children under 6 months: ask a doctor
Sun protection measures: Spending time in the sun increases your risk of skin cancer and early skin aging. To decrease this risk, regularly use a
sunscreen with a broad spectrum SPF value of 15 or higher and other sun protection measures including:
limit time in the sun, especially from 10 a.m. - 2 p.m.
wear long-sleeved shirts, pants, hats and sunglasses.

Inactive Ingredients:

Alcohol, Aloe Barbadensis Leaf Juice, C12-15 Alkyl Benzoate, Glycerin, C13-14 Isoparaffin, Cyclomethicone, Glyceryl Stearate, Laureth-7, PEG-100 Stearate, Polyacrylamide, Citrullus Lanatus (Watermelon) Fruit Extract, Steareth-21, Synthetic Beeswax, Dimethicone, Olea Europaea (Olive) Fruit Oil, Helianthus Annuus (Sunflower) Seed Oil, Camellia Sinensis (Green Tea) Leaf Extract, Chamomilla Recutita (Matricaria) Flower Extract, Cucumis Sativus (Cucumber) Fruit Extract, Daucus Carota Sativa (Carrot) Extract, Glycyrrhiza Glabra (Licorice) Extract, Lentinus Edodes (Shiitake Mushroom) Extract, Macrocystis Pyrifera (Kelp) Extract, Pisum Sativum (Pea) Extract, Caprylyl Glycol, Castor Oil Phosphate, Sodium Benzoate, Potassium Sorbate, Annatto, Dipotassium Glycyrrhizinate, Disodium EDTA, Ferulic Acid, Maltodextrin, Phyllanthus Emblica Fruit Extract, Sodium Hyaluronate, Tetrahydro Curcuminoids, Sorbic Acid, Tetrahexyldecyl Ascorbate, Phospholipids, Retinyl Palmitate, Tocopheryl Acetate, Ascorbyl Palmitate, Tocopherol, Sodium Dehydroacetate, Phenoxyethanol, water.